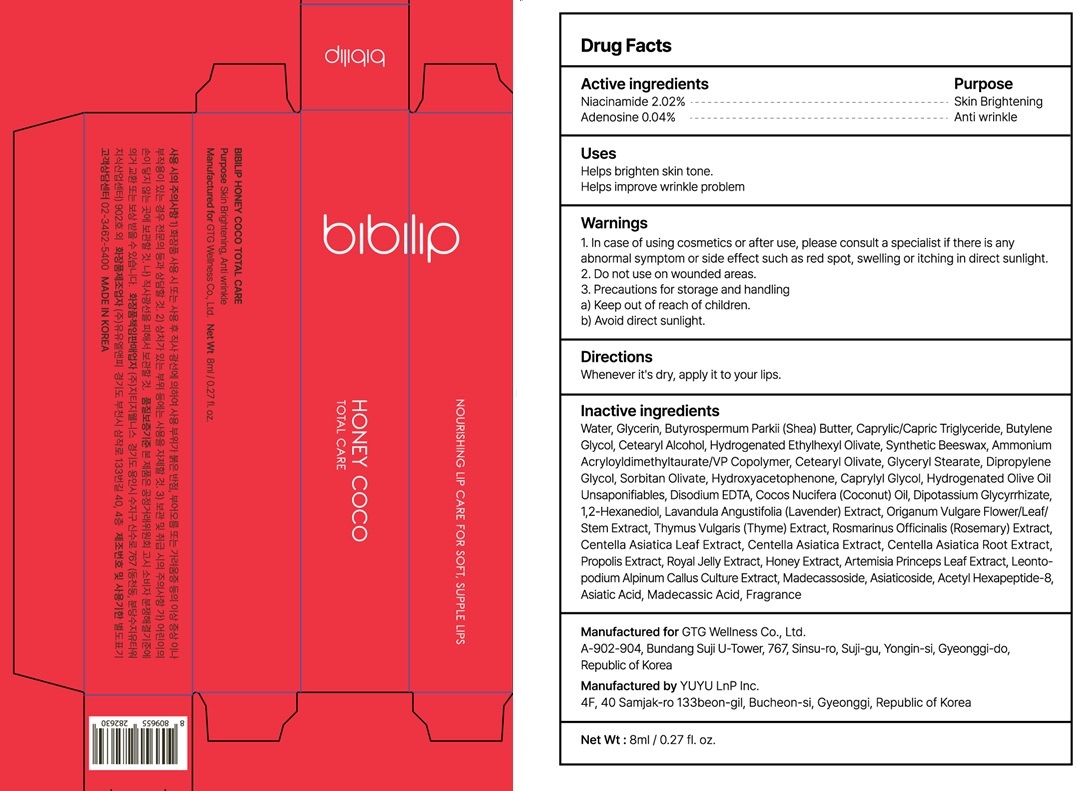 DRUG LABEL: BIBILIP HONEY COCO TOTAL CARE
NDC: 71080-0016 | Form: LIQUID
Manufacturer: GTG Wellness Co., Ltd.
Category: otc | Type: HUMAN OTC DRUG LABEL
Date: 20230525

ACTIVE INGREDIENTS: Niacinamide 0.16 g/8 mL; Adenosine 0.003 g/8 mL
INACTIVE INGREDIENTS: Water; Glycerin

ACTIVE INGREDIENT

Active ingredients: Niacinamide 2.00%, Adenosine 0.04%

INACTIVE INGREDIENT

Inactive ingredients:

Water, Glycerin, Beeswax, Cetearyl Alcohol, 1,2-Hexanediol, Butylene Glycol, Hydrogenated Vegetable Oil, Centella Asiatica Leaf Water, Honey Extract, Propolis Extract, Royal Jelly Extract, Cocos Nucifera (Coconut) Oil, Hydrogenated Coconut Oil, Butyrospermum Parkii (Shea) Butter, Stearic Acid, Diisostearyl Malate, Lavandula Angustifolia (Lavender) Extract, Rosmarinus Officinalis (Rosemary) Extract, Thymus Vulgaris (Thyme) Extract, Origanum Vulgare Flower/Leaf/Stem Extract, Dipotassium Glycyrrhizate, Madecassoside, Behenyl Alcohol, Cetearyl Glucoside, Ammonium Acryloyldimethyltaurate/VP Copolymer, Glucose, Fragrance, Glycine, Serine, Glutamic Acid, Aspartic Acid, Leucine, Alanine, Lysine, Arginine, Tyrosine, Phenylalanine, Valine, Threonine, Proline, Isoleucine, Histidine, Methionine, Cysteine

PURPOSE

Purpose: Skin Brightening, Anti wrinkle

WARNINGS

1. In case of using cosmetics or after use, please consult a specialist if there is any abnormal symptom or side effect such as red spot, swelling or itching in direct sunlight.
2. Do not use on wounded areas.
3. Precautions for storage and handling
a) Keep out of reach of children.
b) Avoid direct sunlight.

KEEP OUT OF REACH OF CHILDREN

Uses

Helps brighten skin tone.
Helps improve wrinkle problem.

Directions

Whenever it's dry, apply it to your lips.